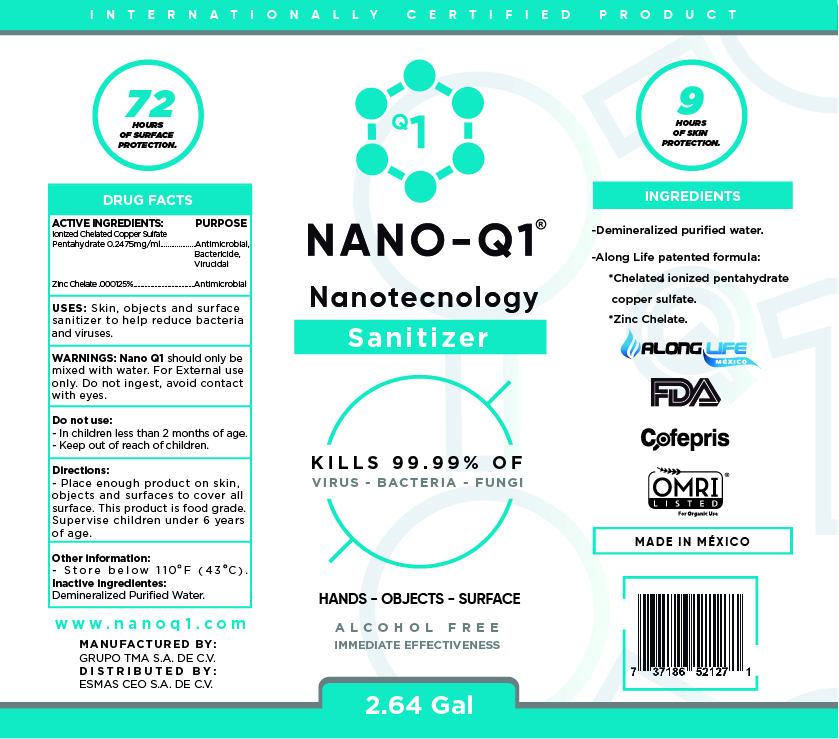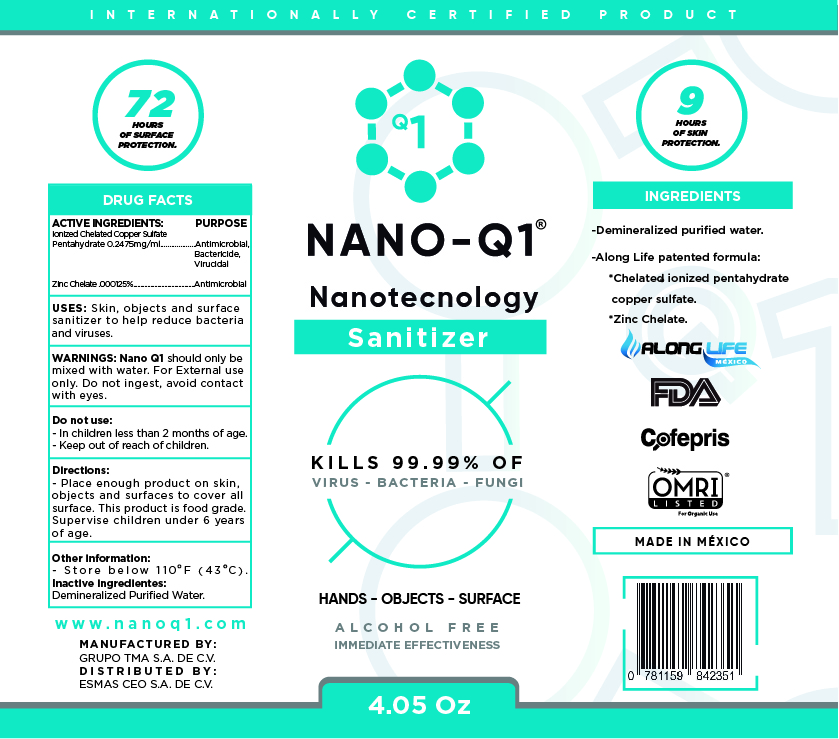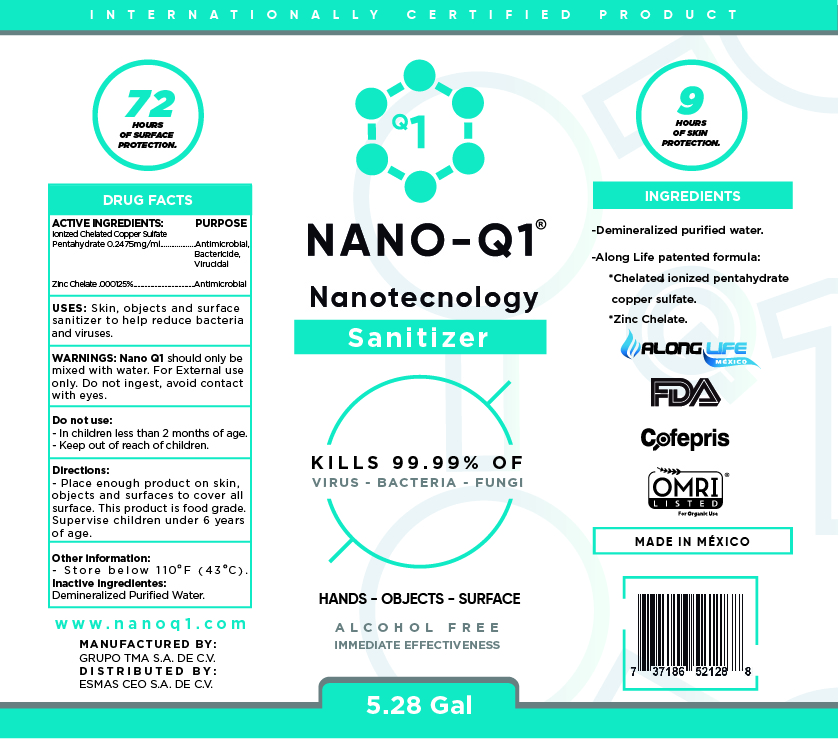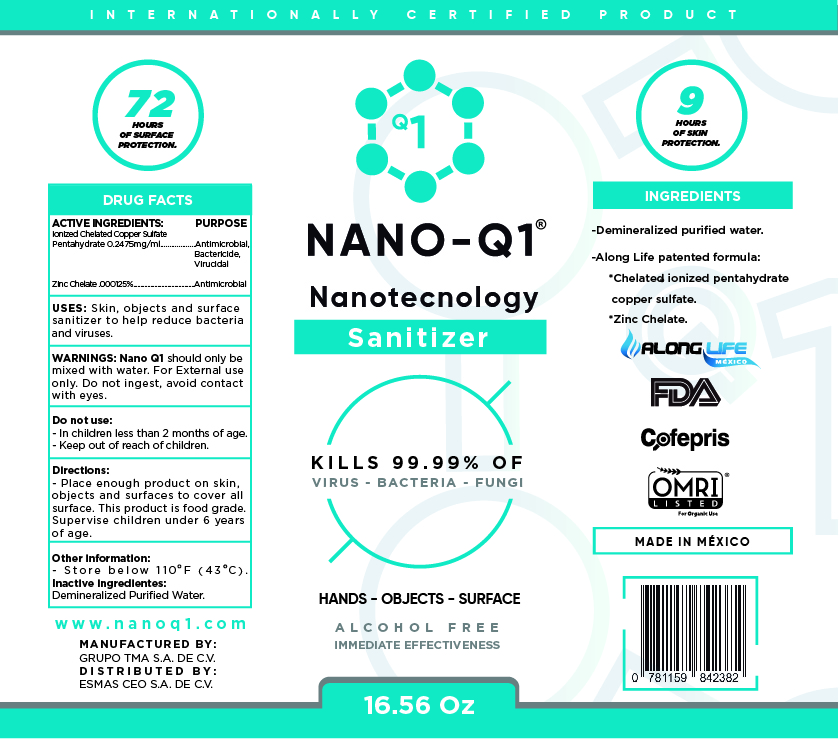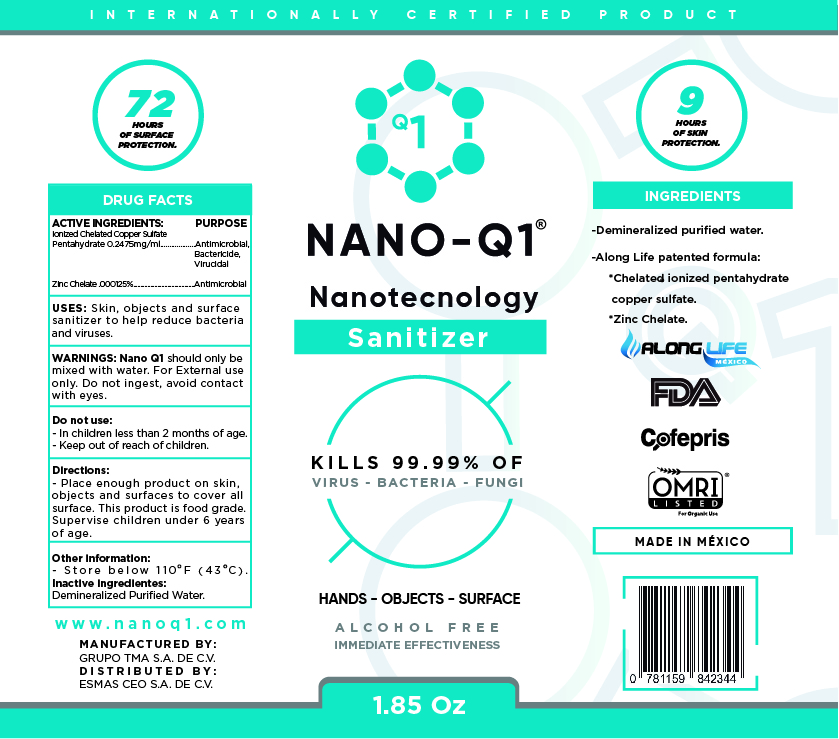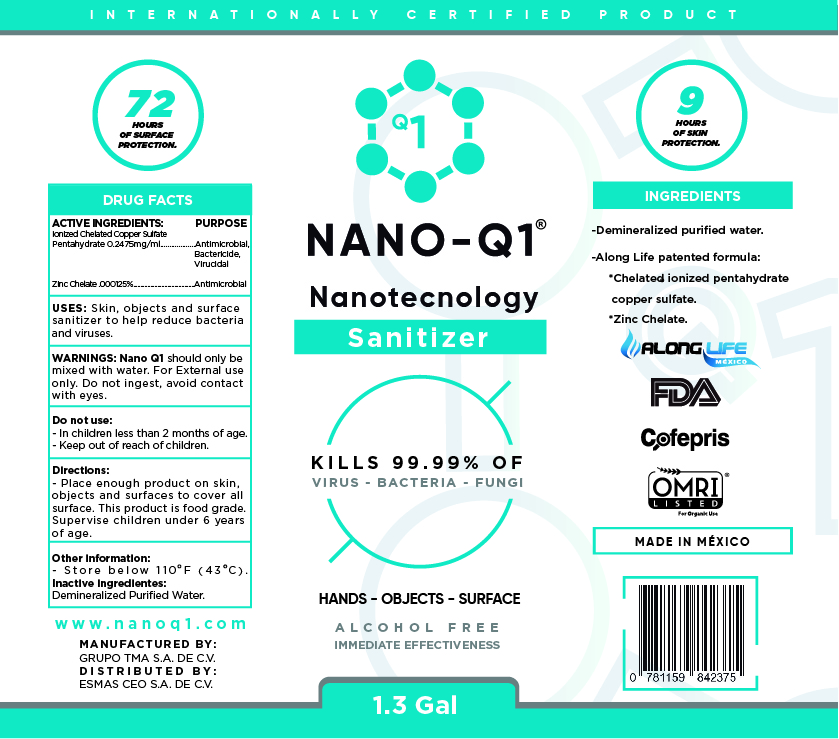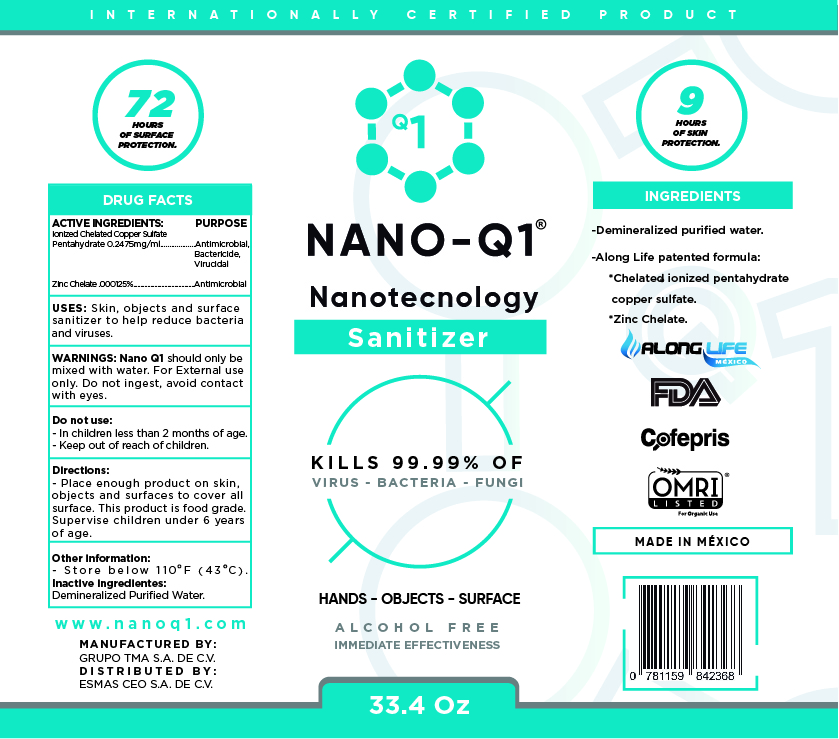 DRUG LABEL: NANO - Q1
NDC: 80224-2000 | Form: SOLUTION
Manufacturer: GRUPO TMA TECNOLOGIAS PARA EL MEJORAMIENTO DEL AGUA S.A. DE C.V.
Category: otc | Type: HUMAN OTC DRUG LABEL
Date: 20210107

ACTIVE INGREDIENTS: CUPRIC SULFATE 0.02475 mg/1 mL
INACTIVE INGREDIENTS: ZINC 0.000125 mL/1 mL; WATER 0.975125 mL/1 mL

NANO - Q1 SANITIZER WITH NANOTECHNOLOGY

ACTIVE INGREDIENT SECTION

Active ingredient Chelated Copper Sulfate Pentahydrate .02475 %

PURPOSE SECTION

Purpose: Antimicrobial, Bactericide, Virucidal

USES

Use[s]

Skin, objects and surface sanitizer to help reduce bacteria and viruses

DOSAGE AND ADMINISTRATION SECTION

Directions

Place enough product on skin, objects and surfaces to cover all surface. This product is food grade. Supervise children under 6 years of age.

WARNINGS AND PRECAUTIONS

Store below 110° F (43°C)

AQUATEC should only be mixed with water. For external use only. Don not ingest, avoid contact with eyes.

WARNINGS

For external use only. Don not ingest, avoid contact with eyes.

DO NOT USE

In children less than 2 months of age.

Keep out of reach of children

INACTIVE INGREDIENTS

Inactive ingredients: Purified demineralized water, Zinc Chelate